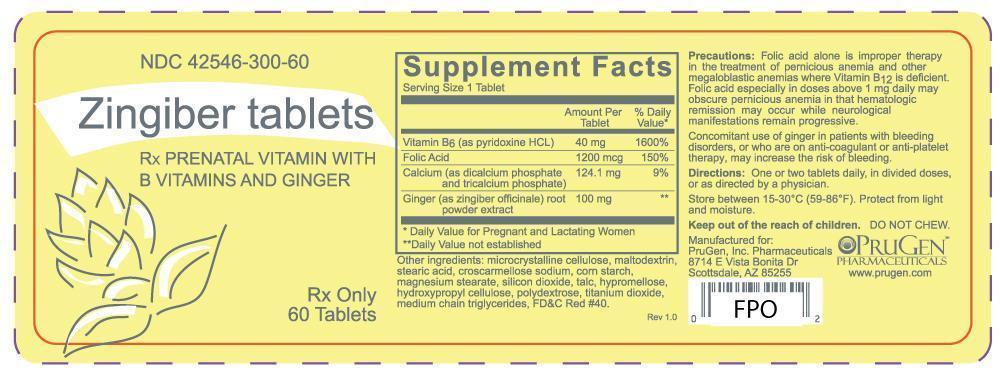 DRUG LABEL: Zingiber
NDC: 42546-300 | Form: TABLET
Manufacturer: PruGen, Inc. Pharmaceuticals
Category: prescription | Type: HUMAN PRESCRIPTION DRUG LABEL
Date: 20130222

ACTIVE INGREDIENTS: PYRIDOXINE 40 mg/1 1; FOLIC ACID 1.2 mg/1 1; CALCIUM 124.1 mg/1 1; GINGER 100 mg/1 1
INACTIVE INGREDIENTS: CELLULOSE, MICROCRYSTALLINE; MALTODEXTRIN; STEARIC ACID; CROSCARMELLOSE SODIUM; STARCH, CORN; MAGNESIUM STEARATE; SILICON DIOXIDE; TALC; HYPROMELLOSES; HYDROXYPROPYL CELLULOSE; POLYDEXTROSE; TITANIUM DIOXIDE; MEDIUM-CHAIN TRIGLYCERIDES; FD&C RED NO. 40

Zingiber

WARNINGS AND PRECAUTIONS

Folic acid alone is improper therapy in the treatment of pernicious anemia and other megaloblastic anemias where Vitamin B12 is deficient. Folic acid especially in doses above 1 mg daily may obscure pernicious anemia in that hematologic remission may occur while neurological manifestations remain progressive.

Concomitant use of ginger in patients with bleeding disorders, or who are on anti-coagulant or anti-platelet therapy, may increase the risk of bleeding.

DESCRIPTION

Each pink tablet contains:

Vitamin B6 (pyridoxine hydrochloride, USP) 40 mg

Folic Acid, USP 1.2 mg

Calcium (as dicalcium phosphate and tricalcium phosphate) 124.1 mg

Ginger (zingiber officinale) root powder extract 100 mg

Other ingredients: microcrystalline cellulose, maltodextrin, stearic acid, croscarmellose sodium, corn starch, magnesium stearate, silicon dioxide, talc, hypromellose, hydroxypropyl cellulose, polydextrose, titanium dioxide, medium chain triglycerides, FD&C Red #40.

DOSAGE AND ADMINISTRATION

One or two tablets daily, in divided doses, or as directed by a physician.

HOW SUPPLIED

Store between 15-30°C (59-86°F). Protect from light and moisture.

Keep out of the reach of children.

DO NOT CHEW.

Manufactured for:

PruGen, Inc. Pharmaceuticals

8714 E Vista Bonita Dr

Scottsdale, AZ 85255

PACKAGE LABEL

NDC 42546-300-60

Zingiber Tablets

Rx prenatal vitamin with B vitamins and ginger

Rx Only

60 tablets